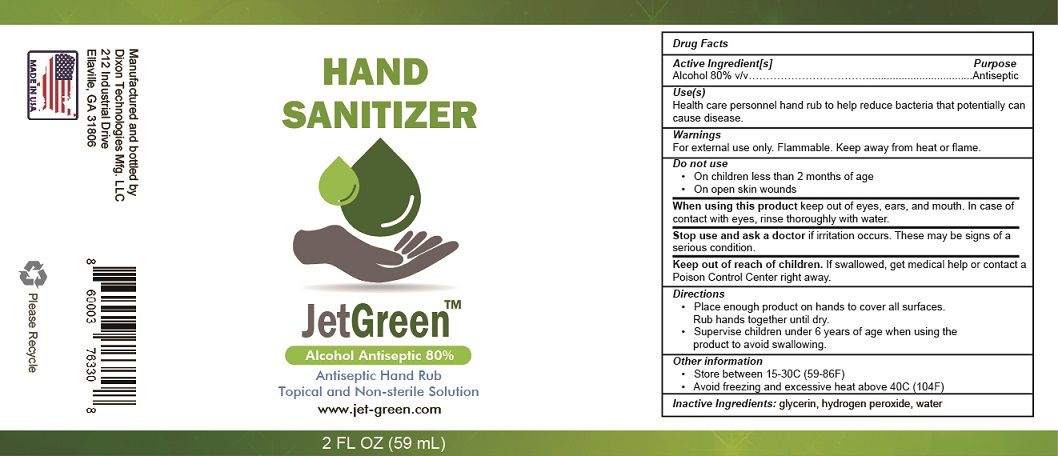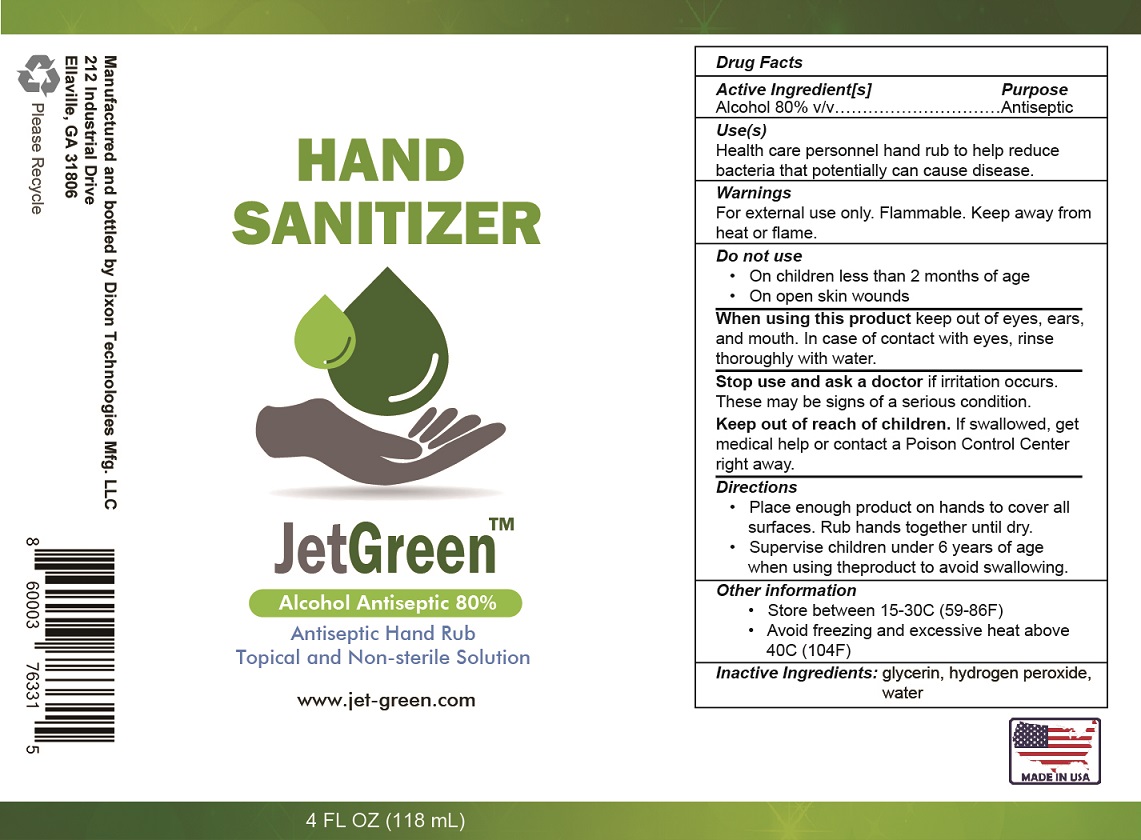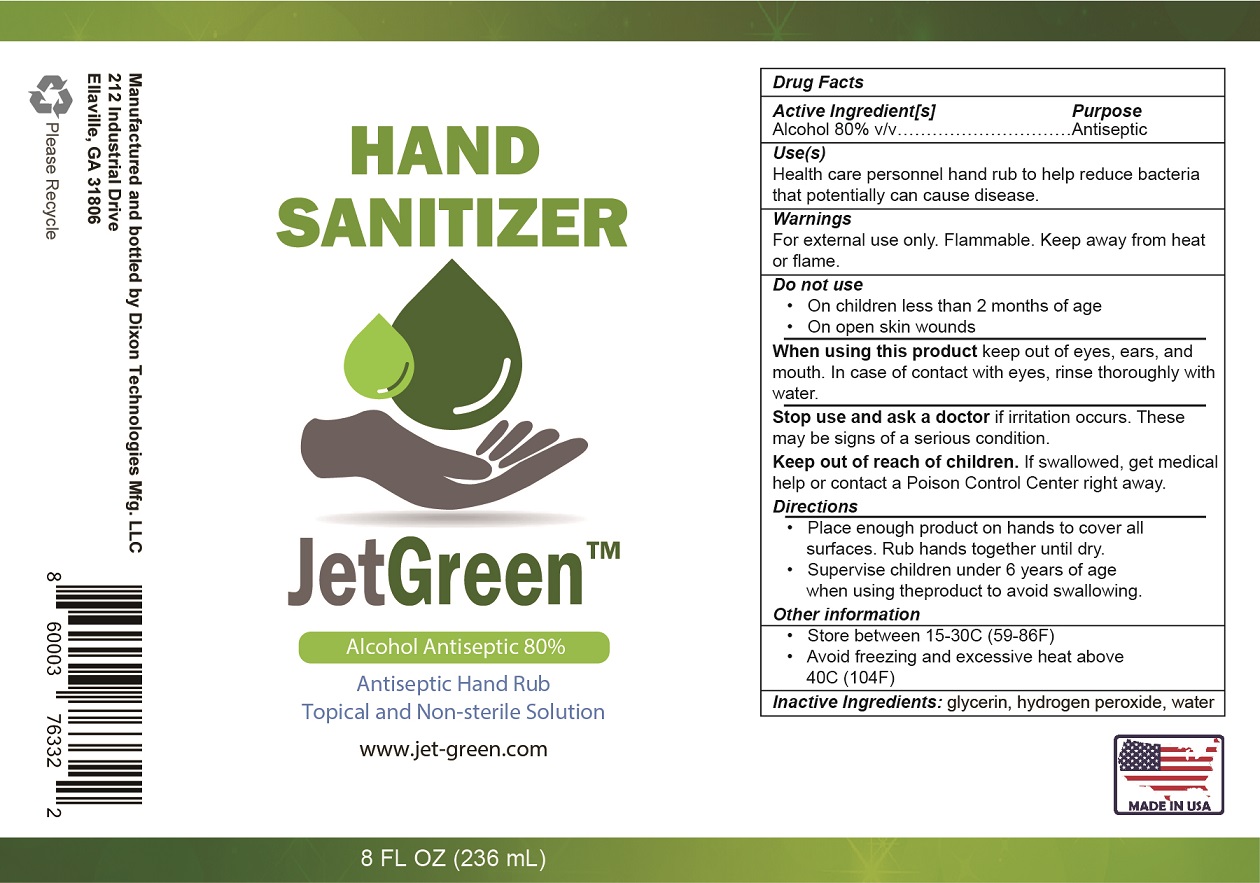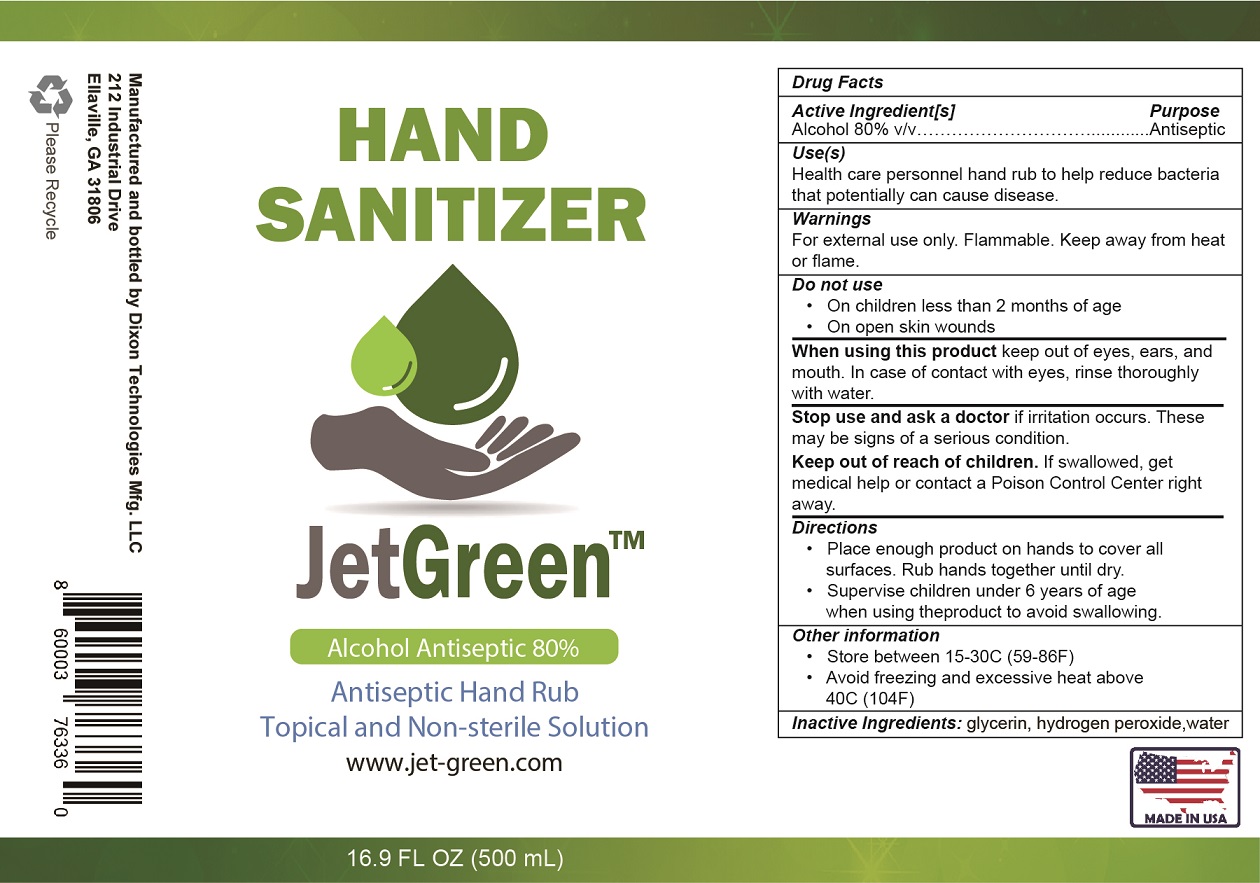 DRUG LABEL: Jet Green Hand Sanitizer
NDC: 78592-001 | Form: LIQUID
Manufacturer: Dixon Technology & Manufacturing LLC
Category: otc | Type: HUMAN OTC DRUG LABEL
Date: 20200701

ACTIVE INGREDIENTS: ALCOHOL 0.8 mL/1 mL
INACTIVE INGREDIENTS: GLYCERIN; HYDROGEN PEROXIDE; WATER

Jet Green Hand Sanitizer

Active Ingredient[S]

Alcohol 80% v/v

Purpose

Antiseptic

Use(s)

Health care personnel hand rub to help reduce bacteria that potentially can cause disease.

Warnings

For external use only. Flammable. Keep away from heat or flame.

Do not use

- On children less than 2 months of age
- On open skin wounds

When using this product

keep out of eyes, ears, and mouth. In case of contact with eyes, rinse thoroughly with water.

Stop use and ask a doctor

if irritation occurs. These may be signs of a serious condition.

Keep out of reach of children.

If swallowed, get medical help or contact a Poison Control Center right away.

Directions

- Place enough product on hands to cover all surfaces. Rub hands together until dry.
- Supervise children under 6 years of age when using the product to avoid swallowing.

Other information

- Store between 15-30C (59-86F)
- Avoid freezing and excessive heat above 40C (104F)

Inactive Ingredients:

glycerin, hydrogen peroxide, water